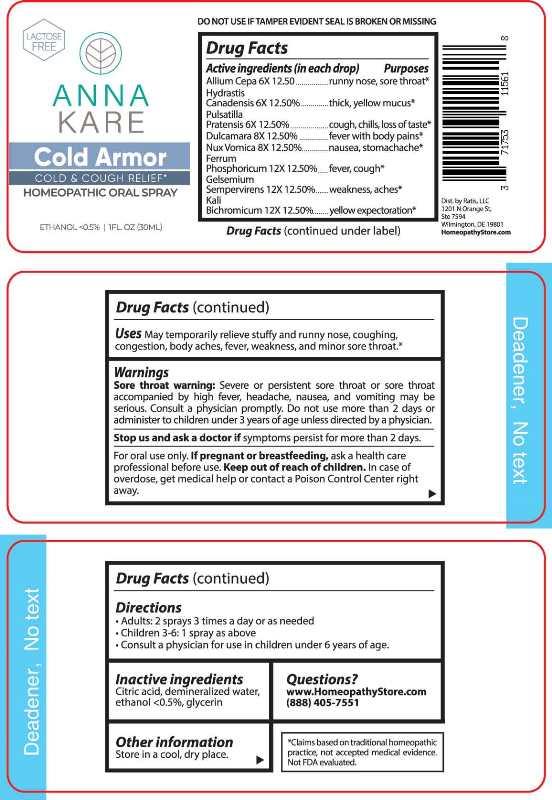 DRUG LABEL: Cold Armor
NDC: 71753-1156 | Form: SPRAY
Manufacturer: Ratis, LLC
Category: homeopathic | Type: HUMAN OTC DRUG LABEL
Date: 20230526

ACTIVE INGREDIENTS: ONION 6 [hp_X]/1 mL; GOLDENSEAL 6 [hp_X]/1 mL; PULSATILLA PRATENSIS WHOLE 6 [hp_X]/1 mL; SOLANUM DULCAMARA TOP 8 [hp_X]/1 mL; STRYCHNOS NUX-VOMICA SEED 8 [hp_X]/1 mL; FERROSOFERRIC PHOSPHATE 12 [hp_X]/1 mL; GELSEMIUM SEMPERVIRENS ROOT 12 [hp_X]/1 mL; POTASSIUM DICHROMATE 12 [hp_X]/1 mL
INACTIVE INGREDIENTS: WATER; ALCOHOL; CITRIC ACID MONOHYDRATE; GLYCERIN

DRUG FACTS:

ACTIVE INGREDIENTS:

(in each drop) Allium Cepa 6X 12.50%, Hydrastis Canadensis 6X 12.50%, Pulsatilla Pratensis 6X 12.50%, Dulcamara 8x 12.50%, Nux Vomica 8x 12.50%, Ferrum Phosphoricum 12X 12.50%, Gelsemium Sempervirens 12X 12.50%, Kali Bichromicum 12X 12.50%

PURPOSES:

Allium Cepa – runny nose, sore throat,* Hydrastis Canadensis – thick , yellow mucus,* Pulsatilla Pratensis – cough, chills, loss of taste,* Dulcamara – fever with body pains,* Nux Vomica – nausea, stomachache,* Ferrum Phosphoricum – fever, cough,* Gelsemium Sempervirens – weakness, aches,* Kali Bichromicum – yellow expectoration.*

USES:

May temporariy relieve stuffy and runny nose, coughing, congestion, body aches, fever, weakness, and minor sore throat.*

* Claims based on traditional homeopathic practice, not accepted medical evidence. Not FDA evaluated.

WARNINGS:

Sore throat warning: Severe or persistent sore throat or sore throat accompanied by high fever, headache, nausea, and vomiting may be serious. Consult a physician promptly. Do not use more than 2 days or administer to children under 3 years of age unless directed by a physician.

Stop use and ask a doctor if symptoms persist for more than 2 days.

For oral use only. If pregnant or breast-feeding, ask a health care professional before use.

Keep out of reach of children. In case of overdose, get medical help or contact a Poison Control center right away.

DO NOT USE IF TAMPER EVIDENT SEAL IS BROKEN OR MISSING

KEEP OUT OF REACH OF CHILDREN:

In case of overdose, get medical help or contact a Poison Control center right away.

DIRECTIONS:

• Adults: 2 sprays 3 times a day or as needed

• Children 3-6: 1 spray as above

• Consult a physician for use in children under 6 years of age.

Store in a cool, dry place

INACTIVE INGREDIENTS:

Citric acid, demineralized water, ethanol <0.5%, glycerin.

QUESTIONS:

www.HomeopathyStore.com

(888) 405-7551

Dist. by Ratis, LLC

1201 N Orange St,

Ste 7594

Wilmington, DE 19801

PACKAGE LABLE DISPLAY:

LACTOSE FREE

ANNA

KARE

Cold Armor

COLD & COUGH RELIEF*

HOMEOPATHIC ORAL SPRAY

1FL. OZ (30ML)